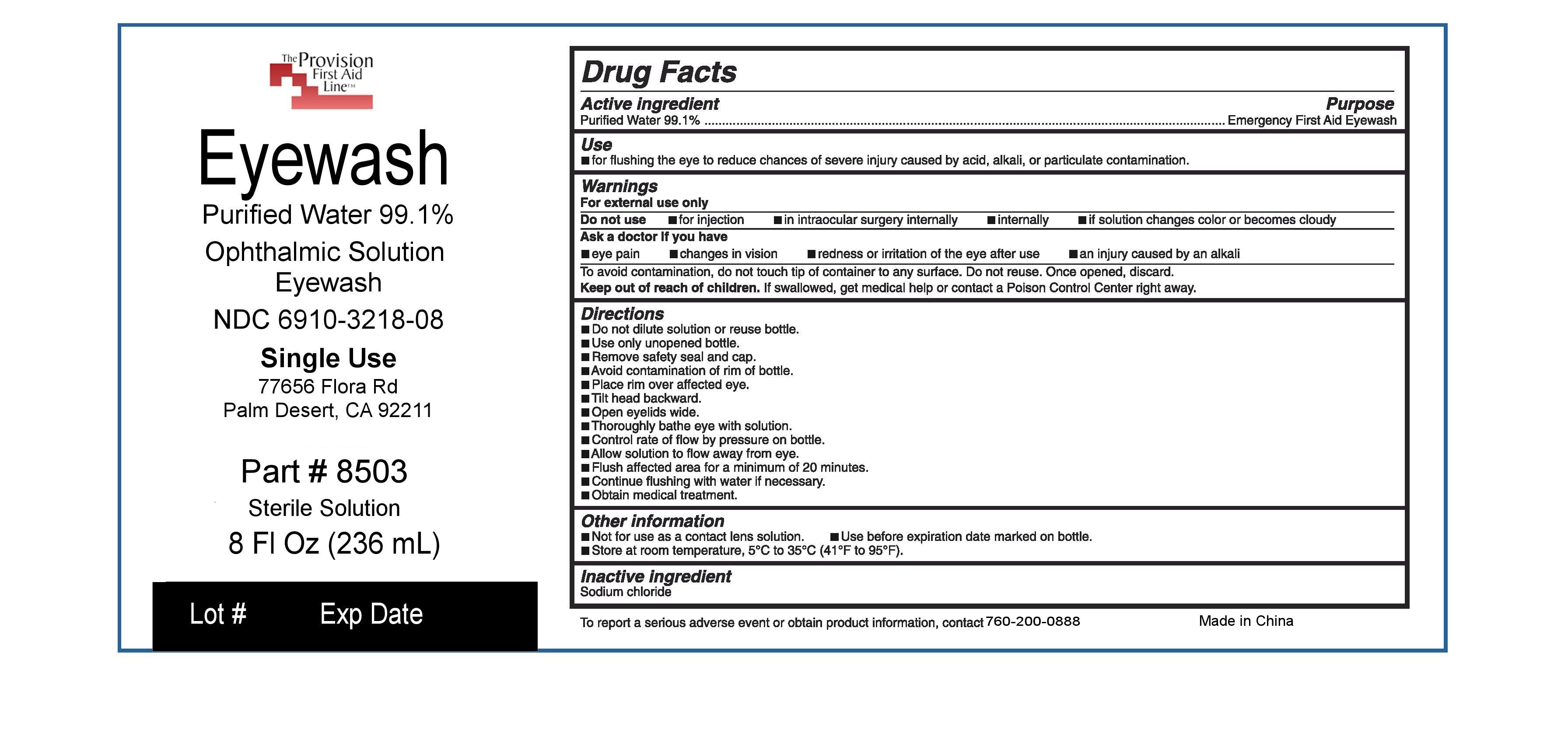 DRUG LABEL: Eye Wash
NDC: 69103-2180 | Form: LIQUID
Manufacturer: Provision Medical Products
Category: otc | Type: HUMAN OTC DRUG LABEL
Date: 20171102

ACTIVE INGREDIENTS: WATER 983 mg/1 mL
INACTIVE INGREDIENTS: SODIUM CHLORIDE

Uses:

fOR CLEANSING THE EYE TO HELP RELIEVE IRRITATION OR BURNING BY REMOVING LOOSE FOREIGN MATERIAL

If pregnant or breast-feeding, ask a health

professional before use.

KEEP OUT OF REACH OF CHILDREN. iF SWALLOWED, get medical help or

contact a Poison Control Center right

away.

Warnings:

For external use only.

Do not use if: you experience any open wounds in or near the eye and obtain immediate medical treatment.

If solution changes color or becomes cloudy.

When using this product -To avoid contamination, do not touch tip of container to any surface. Do not reuse. Once opened, discard

Stop use and ask a doctor if you have any of the following: Changes in vision. Eye pain. Condition worsens or persists. Continued redness or irritation of the eye.

Directions:

Flush the affacted eye as needed, controlling the rate of flow of solution by pressure on the bottle.

Inactive Ingredients:

sodium chloride

ACTIVE INGREDIENT-PURIFIED WATER 98.3%

PURPOSE

EYEWASH